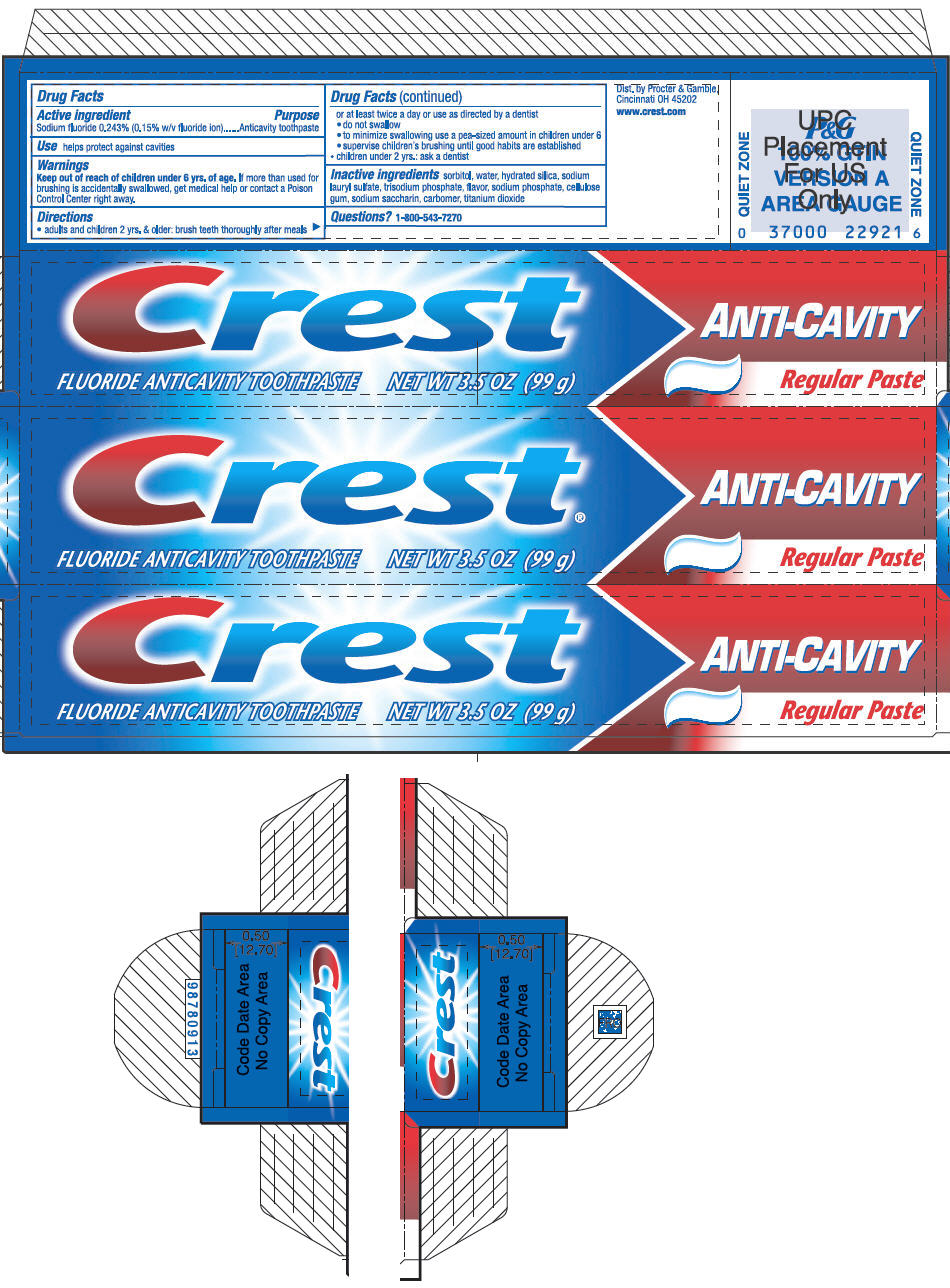 DRUG LABEL: CREST ANTI-CAVITY
NDC: 69772-130 | Form: PASTE, DENTIFRICE
Manufacturer: GENESIS IMPORTS & EXPORTS LLC
Category: otc | Type: HUMAN OTC DRUG LABEL
Date: 20170331

ACTIVE INGREDIENTS: SODIUM FLUORIDE 1.45 g/100 mL
INACTIVE INGREDIENTS: CARBOXYMETHYLCELLULOSE SODIUM; TITANIUM DIOXIDE; EUGENOL; SODIUM LAURYL SULFATE; SODIUM PHOSPHATE; SORBITOL; WATER; HYDRATED SILICA; SACCHARIN SODIUM; XANTHAN GUM

ACTIVE INGREDIENT

Sodium fluoride .243% (.15% w/v flouride ion)

Purpose

Anticavity toothpaste

WARNINGS AND PRECAUTIONS

kEEEP OUT OF REACH OF CHILDREN UNDER 6 YRS OF AGE

KEEP OUT OF REACH OF CHILDREN

KEEP OUT OF THE CHILDREN UNDER 6 YRS OF AGE.

If more than used for brishing is accidentally swallowed, get medical help or contact a poison control center rigth away.

DIRECTIONS

- adults and children 2 yrs & older; brush teeth thoroughly after meals or at least twice a day or use as directed by a dentist
- do not swallow
- to minimize swallowing use a pea-sides amount in children under 6
- supervise children's brushiong until goog habits are established
- children under 2 yrs ask a dentist

INACTIVE INGREDIENTS:

sorbitol,water,hydrated silica, sodium lauryl sulfate, trisosium phosphate, flavor, sodium phospahte, cellulose gum, sodium saccharin, carbomer, titanium dioxide

USE

Helps protect against cavities

KEEP OUT OF REACH OF CHILDREN UNDER 6 YTS OF AGE